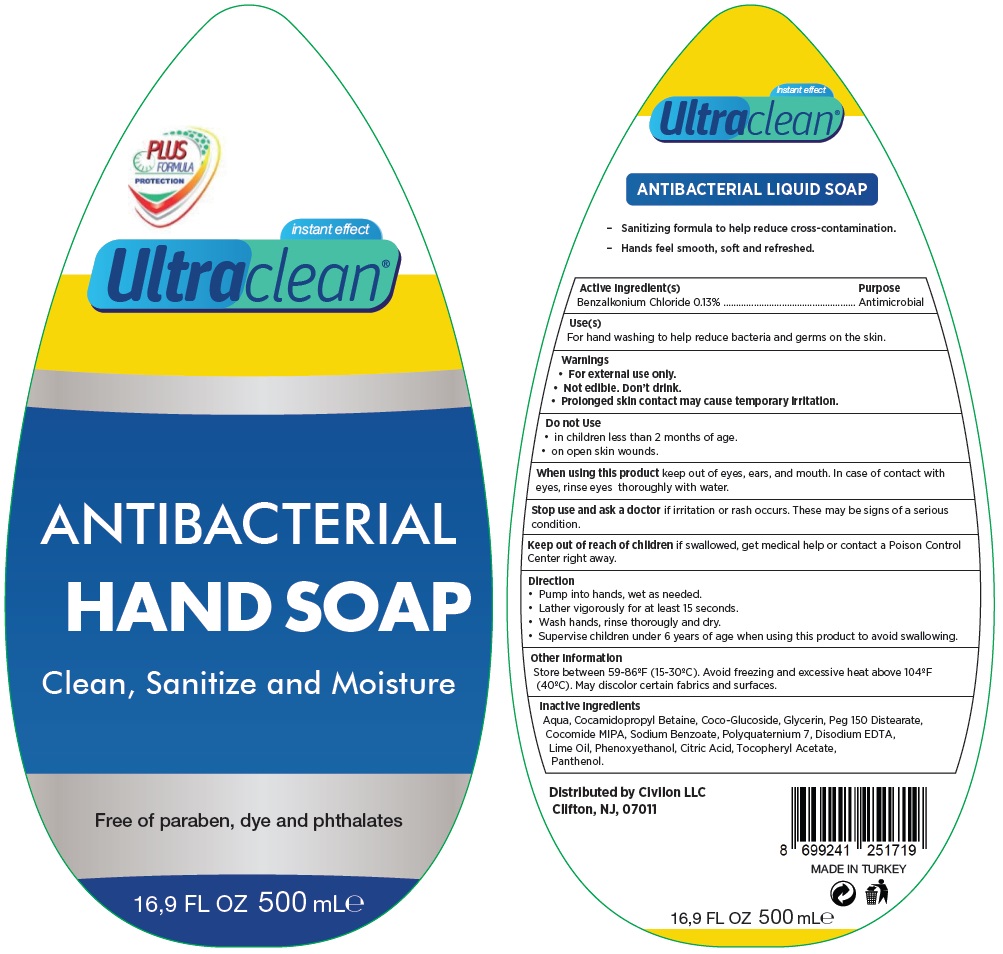 DRUG LABEL: ULTRACLEAN
NDC: 80374-101 | Form: LIQUID
Manufacturer: ASILNUR KIMYA KOZMETIK SANAYI VE TICARET ANONIM SIRKETI
Category: otc | Type: HUMAN OTC DRUG LABEL
Date: 20200901

ACTIVE INGREDIENTS: BENZALKONIUM CHLORIDE 0.13 g/100 mL
INACTIVE INGREDIENTS: WATER; COCAMIDOPROPYL BETAINE; COCO GLUCOSIDE; GLYCERIN; PEG-150 DISTEARATE; COCO MONOISOPROPANOLAMIDE; SODIUM BENZOATE; POLYQUATERNIUM-7 (70/30 ACRYLAMIDE/DADMAC; 1600000 MW); EDETATE DISODIUM ANHYDROUS; LIME OIL; PHENOXYETHANOL; CITRIC ACID MONOHYDRATE; .ALPHA.-TOCOPHEROL ACETATE; PANTHENOL

Ultraclean® ANTIBACTERIAL HAND SOAP

Active Ingredient(s)

Benzalkonium Chloride 0.13%

Purpose

Antimicrobial

Use(s)

For hand washing to help reduce bacteria and germs on the skin.

Warnings

• For external use only.

• Not edible, Don’t drink.

• Prolonged skin contact may cause temporary irritation.

Do not Use

• in children less than 2 months of age.

• on open skin wounds.

When using this product keep out of eyes, ears, and mouth. In case of contact with eyes, rinse eyes thoroughly with water.

Stop use and ask a doctor if irritation or rash occurs. These may be signs of a serious condition.

Keep out of reach of children. If swallowed, get medical help or contact a Poison Control Center right away.

Direction

• Pump into hands, wet as needed.

• Lather vigorously for at least 15 seconds.

• Wash hands, rinse thoroughly and dry.

• Supervise children under 6 years of age when using this product to avoid swallowing.

Other Information

Store between 59-86ºF (15-30ºC). Avoid freezing and excessive heat above 104ºF (40ºC). May discolor certain fabrics and surfaces.

Inactive Ingredients

Aqua, Cocamidopropyl Betaine, Coco-Glucoside, Glycerin, Peg 150 Distearate, Cocomide MIPA,

Sodium Benzoate, Polyquaternium 7, Disodium EDTA, Lime Oil, Phenoxyethanol, Citric Acid,

Tocopheryl Acetate, Panthenol.

PLUS FORMULA PROTECTION

instant effect

Clean, Sanitize and Moisture

Free of paraben, dye and phthalates

ANTIBACTERIAL LIQUID SOAP

– Sanitizing formula to help reduce cross-contamination.

– Hands feel smooth, soft and refreshed.

Distributed by Civilon LLC

Clifton, NJ, 07011

MADE IN TURKEY